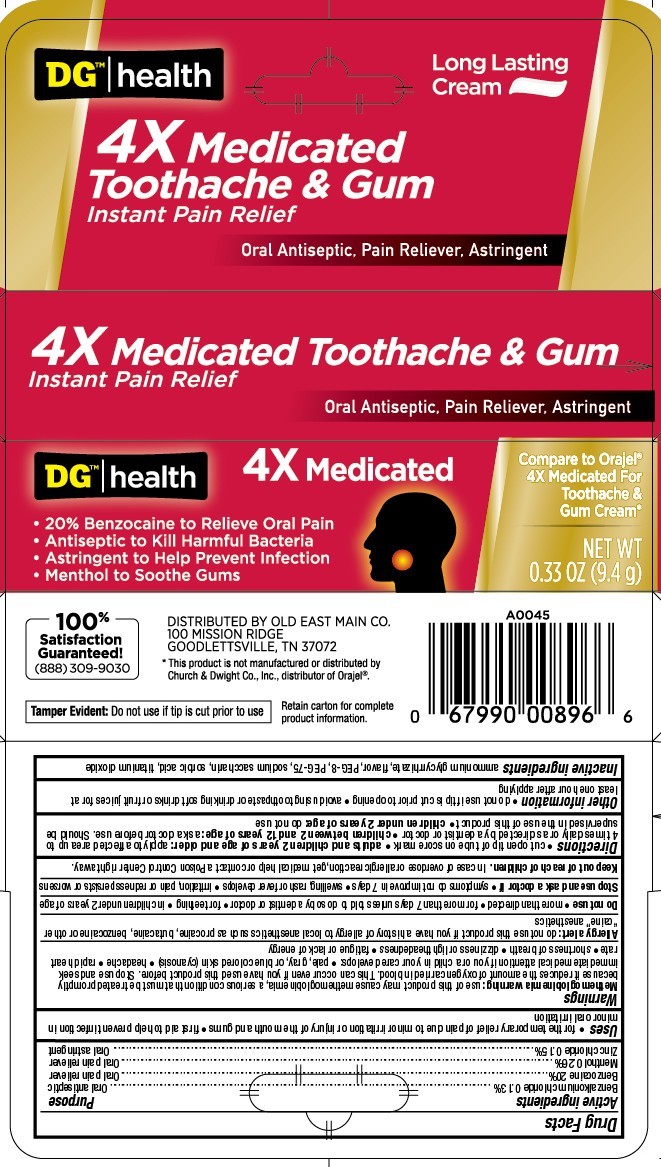 DRUG LABEL: DG 4x Medicated Tooth and Gum Cream
NDC: 55910-660 | Form: CREAM
Manufacturer: Dollar General
Category: otc | Type: HUMAN OTC DRUG LABEL
Date: 20251121

ACTIVE INGREDIENTS: ZINC CHLORIDE 0.15 g/100 g; BENZALKONIUM CHLORIDE 0.13 g/100 g; MENTHOL, UNSPECIFIED FORM 0.26 g/100 g; BENZOCAINE 20 g/100 g
INACTIVE INGREDIENTS: POLYETHYLENE GLYCOL 400; POLYETHYLENE GLYCOL 3350; AMMONIUM GLYCYRRHIZATE; SACCHARIN SODIUM; SORBIC ACID; TITANIUM DIOXIDE

5820606 DG 4x Medicated Toothache & Gum Cream

ACTIVE INGREDIENT

Benzalkonium chloride 0.13%

Benzocaine 20%

Menthol 0.26%

Zinc chloride 0.15%

PURPOSE

Oral antiseptic

Oral pain reliever

Oral pain reliever

Oral astringent

Uses

- for the temporary relief of pain due to minor irritation or njury of the mouth and gums
- first aid to help prevent inceftion in mior oral irritation

WARNINGS

Methemoglobinemia warning: use of this product may cause methemoglobinemia, a serious condition that must be treated promptly because it reduces the amount of oxygen carried in blood. This can occur even if you have used this product before. Stop use and seek immediate medical attention if you or a child in your care develop

- pale, gray, or blue colored skin (cyanosis)
- headache
- rapid heart rate
- shortness of breath
- dizziness or lightheadedness
- fatigue or lack of energy

Allergy alert: do not use this product if you have a history of allergy to local anesthetics such as procaine, butacaine, benzocaine or other "caine" anesthetics

Do not use

- more than directed
- for more than 7 days unless told to do so by a dentist or doctor
- for teething
- in children under 2 years of age

Stop use and ask a doctor if

- symptoms do not improve in 7 days
- swelling, rash or fever develops
- irritation, pain or redness persists or worsens

Keep out reach of children. In case of overdose or allergic reaction, get medical help or contact a Posion Control Center right away.

Keep out of reach of children. In case of overdose, get medical help or contact a Poison Control Center right away.

DOSAGE AND ADMINISTRATION

cut open tip of tube on score mark * adults and children 2 years of age and older: apply a small amount of product to teh cavity and around teh gum surrounding the teeth. Use up to 4 times daily or as directed by a dentist or doctor * children under 12 years of age should be supervised in teh use of this product * children under 2 years of age: do not use

Other information

- do not use if tip is cut prior to opening
- avoid using toothpaste or drinking soft drinks or fruit juices for at least one hour after applying

INACTIVE INGREDIENT

ammonium glycyrrhizate, flavor, PEG-8, PEG-75, sodium saccharin, sorbic acid, titanium dioxide